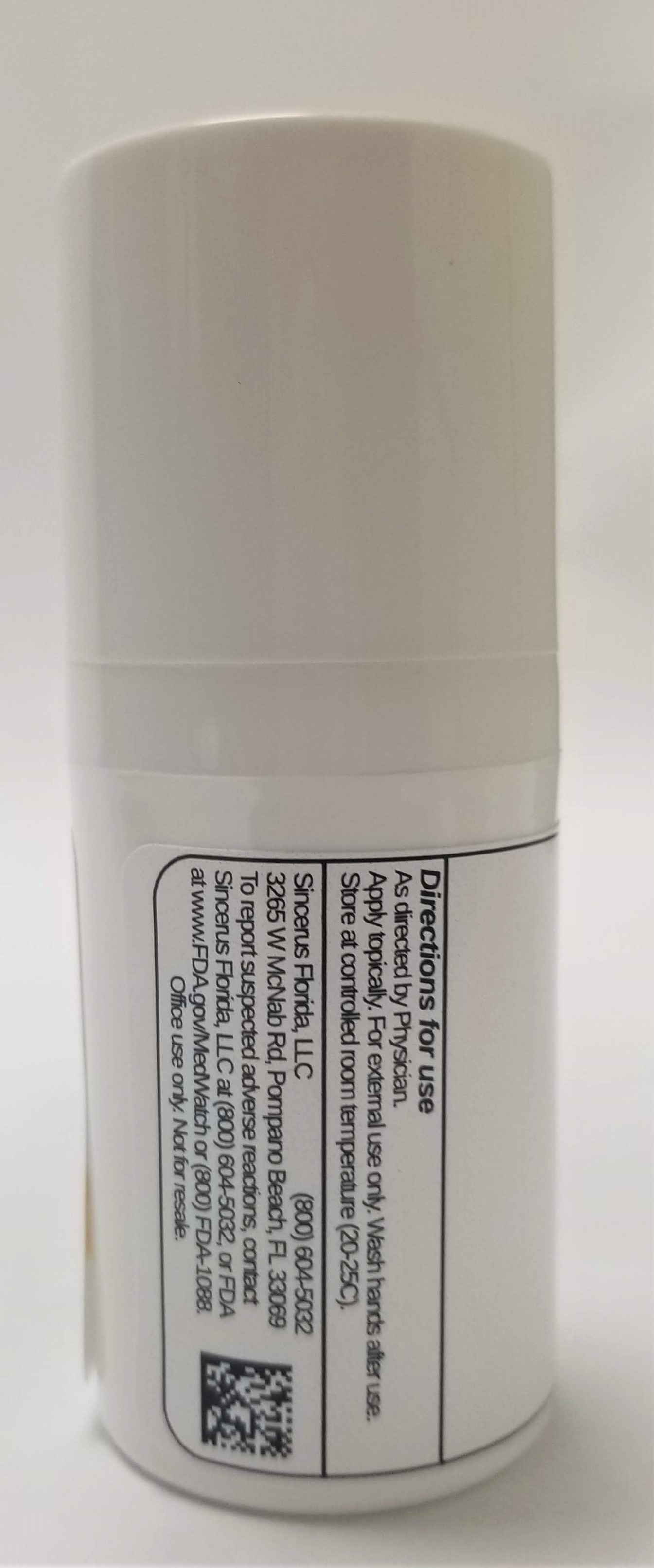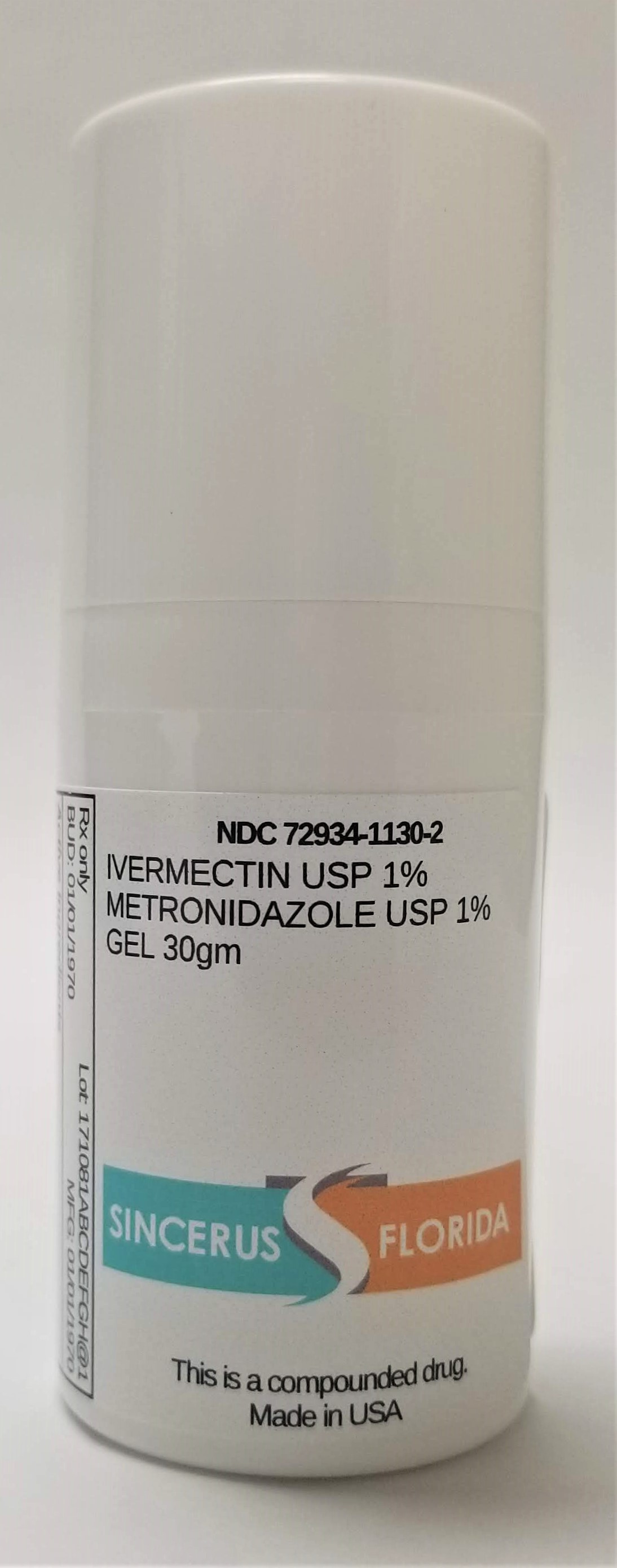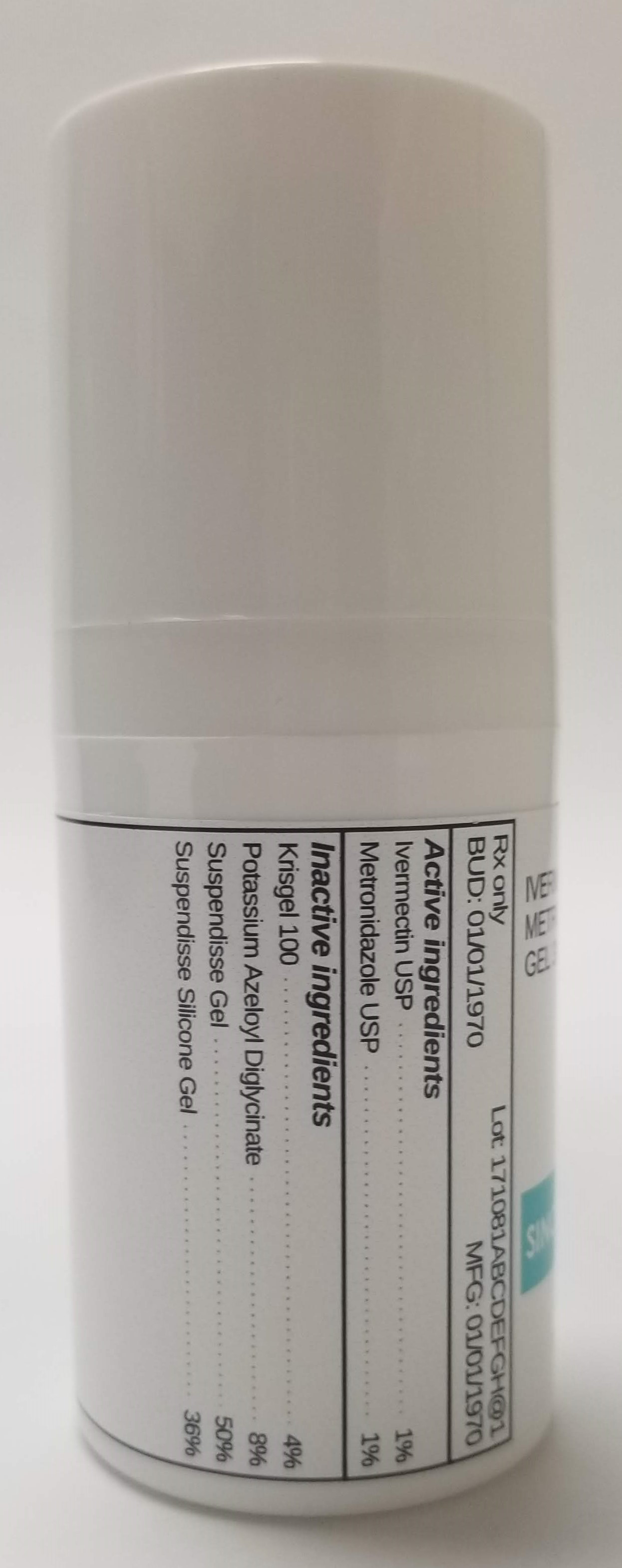 DRUG LABEL: IVERMECTIN 1% / METRONIDAZOLE 1%
NDC: 72934-1130 | Form: GEL
Manufacturer: Sincerus Florida, LLC
Category: prescription | Type: HUMAN PRESCRIPTION DRUG LABEL
Date: 20190424

ACTIVE INGREDIENTS: METRONIDAZOLE 1 g/100 g; IVERMECTIN 1 g/100 g

IVERMECTIN 1% / METRONIDAZOLE 1%